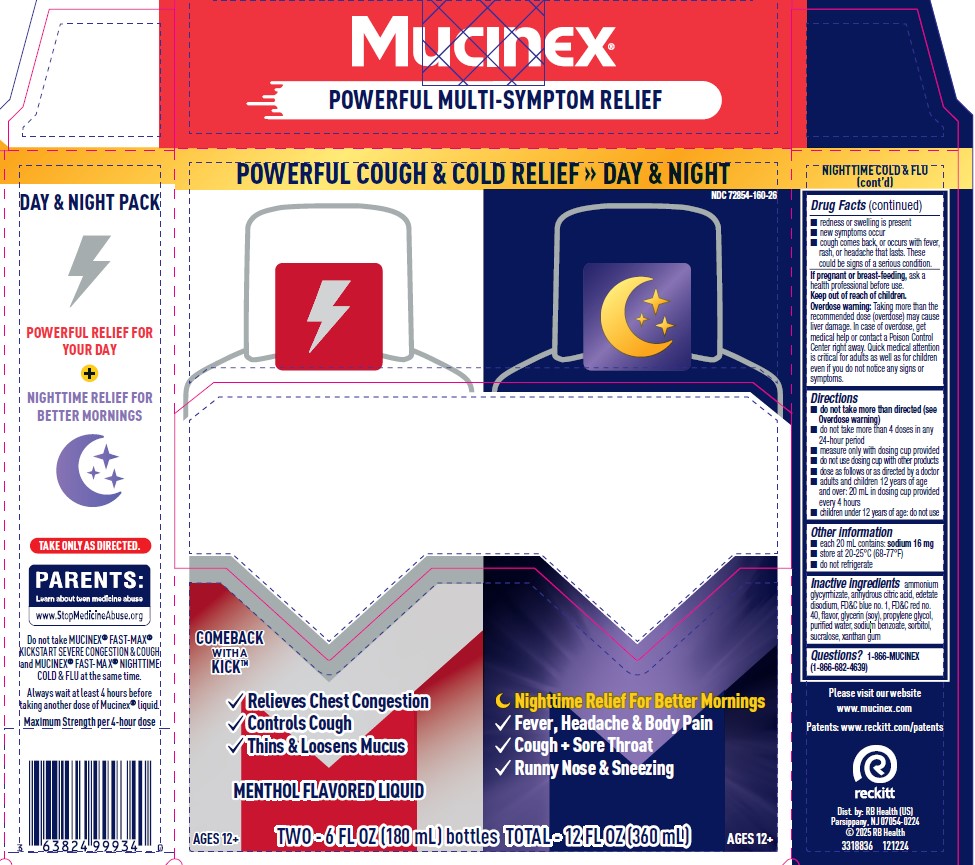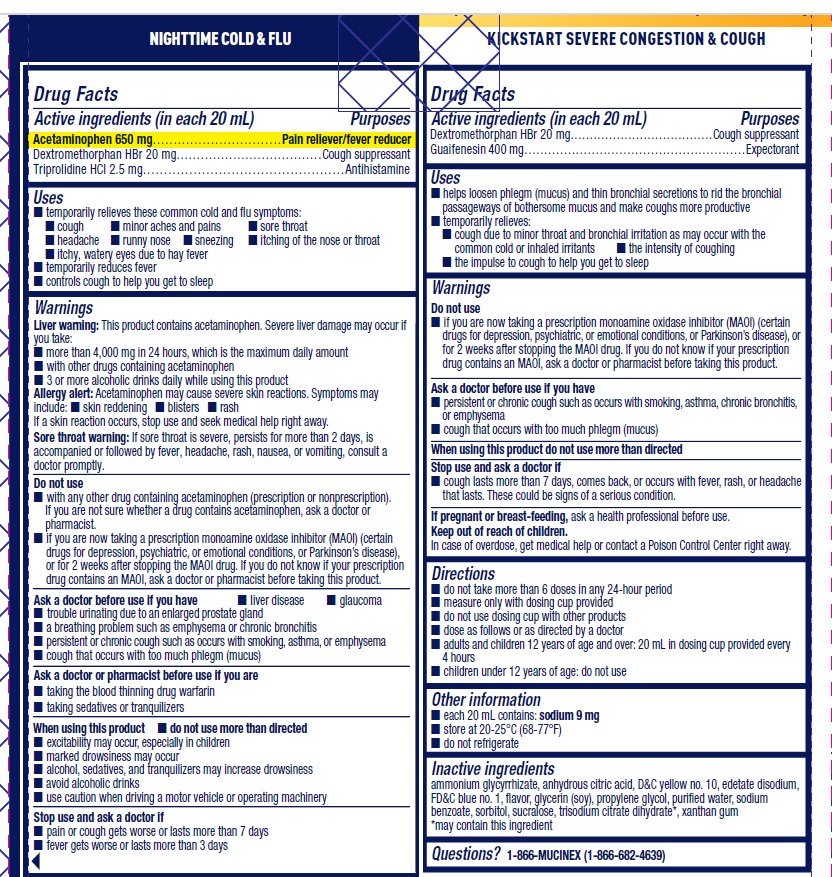 DRUG LABEL: Mucinex Fast-Max Kickstart Severe Congestion and Cough and Mucinex Fast-Max Nighttime Cold and Flu
NDC: 72854-160 | Form: KIT | Route: ORAL
Manufacturer: RB Health (US) LLC
Category: otc | Type: HUMAN OTC DRUG LABEL
Date: 20250512

ACTIVE INGREDIENTS: ACETAMINOPHEN 650 mg/20 mL; TRIPROLIDINE HYDROCHLORIDE 2.5 mg/20 mL; DEXTROMETHORPHAN HYDROBROMIDE 20 mg/20 mL; GUAIFENESIN 400 mg/1 1; DEXTROMETHORPHAN HYDROBROMIDE 20 mg/1 1
INACTIVE INGREDIENTS: FD&C BLUE NO. 1; AMMONIUM GLYCYRRHIZATE; FD&C RED NO. 40; WATER; SORBITOL; EDETATE DISODIUM; SODIUM BENZOATE; GLYCERIN; ANHYDROUS CITRIC ACID; SUCRALOSE; XANTHAN GUM; PROPYLENE GLYCOL; ANHYDROUS CITRIC ACID; D&C YELLOW NO. 10; FD&C BLUE NO. 1; SUCRALOSE; XANTHAN GUM; TRISODIUM CITRATE DIHYDRATE; EDETATE DISODIUM; WATER; AMMONIUM GLYCYRRHIZATE; GLYCERIN; PROPYLENE GLYCOL; SODIUM BENZOATE; SORBITOL

Active ingredients
(in each 20 mL)
Dextromethorphan HBr 20 mg
Guaifenesin 400 mg

Acetaminophen 650 mg
Dextromethorphan HBr 20 mg
Triprolidine HCl 2.5 mg

PURPOSE

Dextromethorphan HBr » Cough Suppressant
Guaifenesin » Expectorant

Acetaminophen » Pain reliever/fever reducer
Dextromethorphan » Cough suppressant
Triprolidine HCl » Antihistamine

Uses

■ helps loosen phlegm (mucus) and thin
bronchial secretions to rid the bronchial
passageways of bothersome mucus and
make coughs more productive
■ temporarily relieves:
■ cough due to minor throat and
bronchial irritation as may occur with
the common cold or inhaled irritants
■ the intensity of coughing
■ the impulse to cough to help you get
to sleep

■ temporarily relieves these common cold and flu symptoms:
■ cough ■ minor aches and pains ■ sore throat
■ headache ■ runny nose ■ sneezing ■ itching of the nose or throat
■ itchy, watery eyes due to hay fever
■ temporarily reduces fever
■ controls cough to help you get to sleep

Do not use
■ if you are now taking a prescription
monoamine oxidase inhibitor (MAOI) (certain
drugs for depression, psychiatric, or
emotional conditions, or Parkinson’s disease),
or for 2 weeks after stopping the MAOI drug.
If you do not know if your prescription drug
contains an MAOI, ask a doctor or
pharmacist before taking this product.

Ask a doctor before use if you have
■ persistent or chronic cough such as occurs
with smoking, asthma, chronic bronchitis, or
emphysema
■ cough that occurs with too much phlegm (mucus)

When using this product do not use more
than directed

Stop use and ask a doctor if
■ cough lasts more than 7 days, comes back, or
occurs with fever, rash, or headache that lasts.
These could be signs of a serious condition.

Liver warning: This product contains acetaminophen. Severe liver damage may occur if
you take:
■ more than 4,000 mg in 24 hours, which is the maximum daily amount
■ with other drugs containing acetaminophen
■ 3 or more alcoholic drinks daily while using this product
Allergy alert: Acetaminophen may cause severe skin reactions. Symptoms may
include: ■ skin reddening ■ blisters ■ rash
If a skin reaction occurs, stop use and seek medical help right away.
Sore throat warning: If sore throat is severe, persists for more than 2 days, is
accompanied or followed by fever, headache, rash, nausea, or vomiting, consult a
doctor promptly.
Do not use
■ with any other drug containing acetaminophen (prescription or nonprescription).
If you are not sure whether a drug contains acetaminophen, ask a doctor or
pharmacist.
■ if you are now taking a prescription monoamine oxidase inhibitor (MAOI) (certain
drugs for depression, psychiatric, or emotional conditions, or Parkinson’s disease),
or for 2 weeks after stopping the MAOI drug. If you do not know if your prescription
drug contains an MAOI, ask a doctor or pharmacist before taking this product.
Ask a doctor before use if you have ■ liver disease ■ glaucoma
■ trouble urinating due to an enlarged prostate gland
■ a breathing problem such as emphysema or chronic bronchitis
■ persistent or chronic cough such as occurs with smoking, asthma, or emphysema
■ cough that occurs with too much phlegm (mucus)
Ask a doctor or pharmacist before use if you are
■ taking the blood thinning drug warfarin
■ taking sedatives or tranquilizers
When using this product ■ do not use more than directed
■ excitability may occur, especially in children
■ marked drowsiness may occur
■ alcohol, sedatives, and tranquilizers may increase drowsiness
■ avoid alcoholic drinks
■ use caution when driving a motor vehicle or operating machinery
Stop use and ask a doctor if
■ pain or cough gets worse or lasts more than 7 days
■ fever gets worse or lasts more than 3 days

■ redness or swelling is present
■ new symptoms occur
■ cough comes back, or occurs with fever,
rash, or headache that lasts. These
could be signs of a serious condition.

Directions
■ do not take more than 6 doses in any
24-hour period
■ measure only with dosing cup provided
■ do not use dosing cup with other products
■ dose as follows or as directed by a doctor
■ adults and children 12 years of age and over:
20 mL in dosing cup provided every 4 hours
■ children under 12 years of age: do not use

Directions
■ do not take more than directed (see
Overdose warning)
■ do not take more than 4 doses in any
24-hour period
■ measure only with dosing cup provided
■ do not use dosing cup with other products
■ dose as follows or as directed by a doctor
■ adults and children 12 years of age
and over: 20 mL in dosing cup provided
every 4 hours
■ children under 12 years of age: do not use

Other information
■ each 20 mL contains: sodium 9 mg
■ store at 20-25°C (68-77°F)
■ do not refrigerate

Other information
■ each 20 mL contains: sodium 16 mg
■ store at 20-25°C (68-77°F)
■ do not refrigerate

Keep out of reach of children.
In case of overdose, get medical help or contact a Poison Control Center right away.

Inactive ingredients

ammonium, glycyrrhizate, anhydrous citric acid, D&C yellow
no. 10, edetate disodium, FD&C blue no. 1, flavor,
glycerin (soy), propylene glycol, purified water,
sodium benzoate, sorbitol, sucralose, trisodium
citrate dihydrate*, xanthan gum
*may contain this ingredient

Inactive ingredients ammonium
glycyrrhizate, anhydrous citric acid, edetate
disodium, FD&C blue no. 1, FD&C red no.
40, flavor, glycerin (soy), propylene glycol,
purified water, sodium benzoate, sorbitol,
sucralose, xanthan gum

Questions?
1-866-MUCINEX (1-866-682-4639)